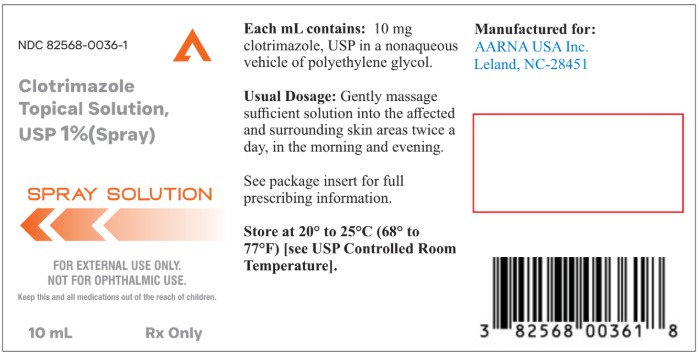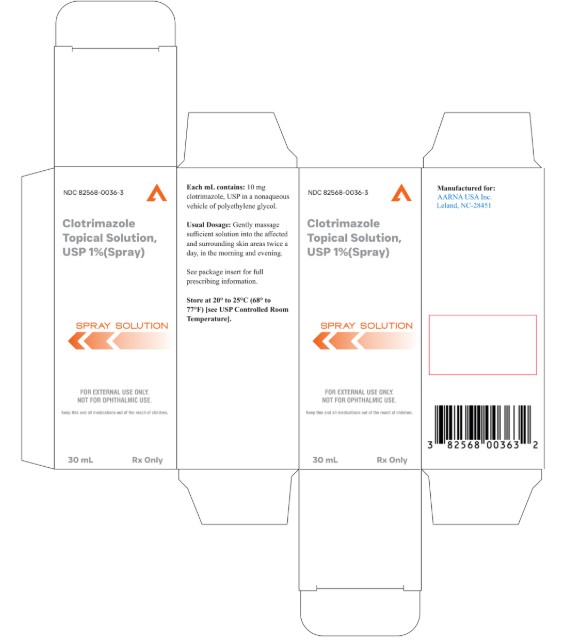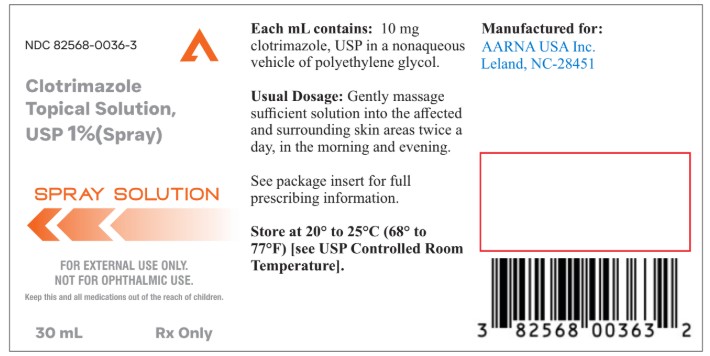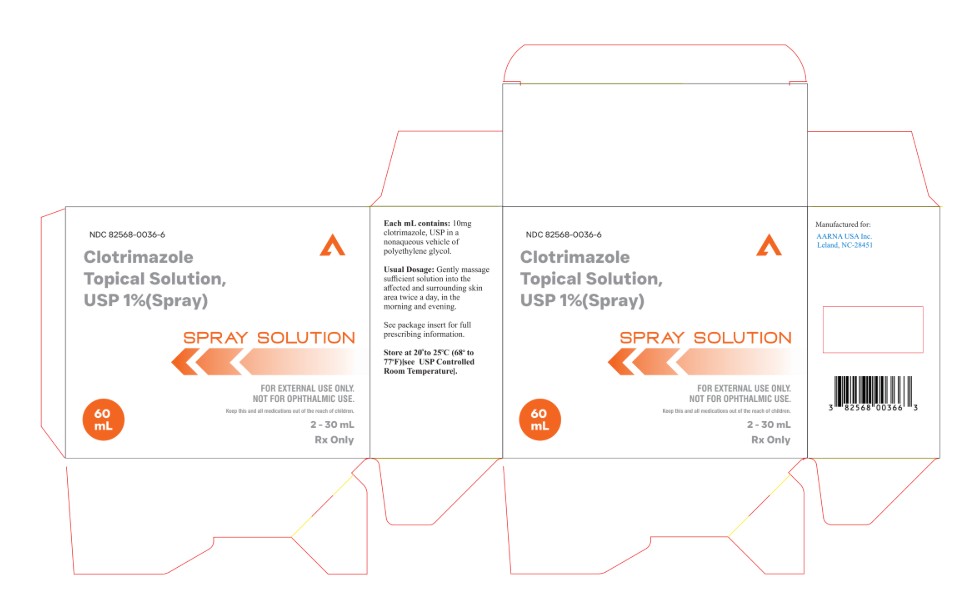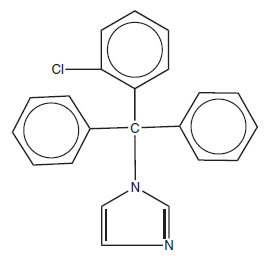 DRUG LABEL: CLOTRIMAZOLE
NDC: 82568-0036 | Form: SPRAY
Manufacturer: AARNA USA INC
Category: prescription | Type: HUMAN PRESCRIPTION DRUG LABEL
Date: 20260227

ACTIVE INGREDIENTS: CLOTRIMAZOLE 10 mg/1 mL
INACTIVE INGREDIENTS: POLYETHYLENE GLYCOL 400; ALCOHOL; CHLOROFORM

Clotrimazole 1% Topical solution spray

FOR EXTERNAL USE ONLY.

NOT FOR OPHTHALMIC USE.

This product is also available without a prescription.

Rx only

DESCRIPTION

Clotrimazole Topical Solution USP, 1% Spray contains 10 mg clotrimazole USP, a synthetic antifungal agent having the chemical name 1-(o-Chloro-α,α-diphenylbenzyl) imidazole with the following structural formula:

Molecular Formula C22H17ClN2

Molecular Weight 344.85

Clotrimazole is an odorless, white crystalline substance. It is practically insoluble in water, sparingly soluble in ether and very soluble in polyethylene glycol 400, ethanol, and chloroform.

Each mL of Clotrimazole Topical Solution, USP 1% Spray contains 10 mg clotrimazole USP in a nonaqueous vehicle of polyethylene glycol 400.

CLINICAL PHARMACOLOGY

Clotrimazole is a broad-spectrum antifungal agent that is used for the treatment of dermal infections caused by various species of pathogenic dermatophytes, yeasts, and Malassezia furfur. The primary action of clotrimazole is against dividing and growing organisms.

In vitro, clotrimazole exhibits fungistatic and fungicidal activity against isolates of Trichophyton rubrum, Trichophyton mentagrophytes, Epidermophyton floccosum, Microsporum canis,and Candida species including Candida albicans. In general, the in vitroactivity of clotrimazole corresponds to that of tolnaftate and griseofulvin against the mycelia of dermatophytes (Trichophyton, Microsporum, and Epidermophyton),and to that of the polyenes (amphotericin B and nystatin) against budding fungi (Candida). Using an in vivo(mouse) and an in vitro(mouse kidney homogenate) testing system, clotrimazole and miconazole were equally effective in preventing the growth of the pseudomycelia and mycelia of Candida albicans.

Strains of fungi having a natural resistance to clotrimazole are rare. Only a single isolate of Candida guilliermondihas been reported to have primary resistance to clotrimazole.

No single-step or multiple-step resistance to clotrimazole has developed during successive passages of Candida albicans and Trichophyton mentagrophytes. No appreciable change in sensitivity was detected after successive passages of isolates of C. albicans, C. krusei, or C. pseudotropicalisin liquid or solid media containing clotrimazole. Also, resistance could not be developed in chemically induced mutant strains of polyene-resistant isolates of C. albicans.

Slight, reversible resistance was noted in three isolates of C. albicanstested by one investigator. There is a single report that records the clinical emergence of a C. albicansstrain with considerable resistance to flucytosine and miconazole, and with cross-resistance to clotrimazole; the strain remained sensitive to nystatin and amphotericin B.

In studies of the mechanism of action, the minimum fungicidal concentration of clotrimazole caused leakage of intracellular phosphorus compounds into the ambient medium with concomitant breakdown of cellular nucleic acids and accelerated potassium efflux. Both these events began rapidly and extensively after addition of the drug.

Clotrimazole appears to be well absorbed in humans following oral administration and is eliminated mainly as inactive metabolites. Following topical and vaginal administration, however, clotrimazole appears to be minimally absorbed.

Six hours after the application of radioactive clotrimazole 1% cream and 1% solution onto intact and acutely inflamed skin, the concentration of clotrimazole varied from 100 mcg/cm^3, in the stratum corneum to 0.5 mcg/cm^3to 1 mcg/cm^3in the stratum reticulare, and 0.1 mcg/cm^3in the subcutis.

No measurable amount of radioactivity (≤ 0.001 mcg/mL) was found in the serum within 48 hours after application under occlusive dressing of 0.5 mL of the solution or 0.8 g of the cream.

Only 0.5% or less of the applied radioactivity was excreted in the urine.

Following intravaginal administration of 100 mg^14C-clotrimazole vaginal tablets to nine adult females, an average peak serum level, corresponding to only 0.03 mcg equivalents/mL of clotrimazole, was reached 1 to 2 days after application. After intravaginal administration of 5 g of 1%^14C-clotrimazole vaginal cream containing 50 mg active drug, to five subjects (one with candidal colpitis), serum levels corresponding to approximately 0.01 mcg equivalents/mL were reached between 8 and 24 hours after application.

INDICATIONS AND USAGE

Prescription Clotrimazole Topical Solution Spray product is indicated for the topical treatment of candidiasis due to Candida albicansand tinea versicolor due to Malassezia furfur.

This formulation is also available as a nonprescription product which is indicated for the topical treatment of the following dermal infections: tinea pedis, tinea cruris, and tinea corporis due to Trichophyton rubrum, Trichophyton mentagrophytes, Epidermophyton fluoccosum, and Microsporum canis.

CONTRAINDICATIONS

Topical antifungal agents are contraindicated in those patients with a history of hypersensitivity to any of the components of the preparation.

WARNINGS

Clotrimazole Topical Solution Spray is not for ophthalmic use.

PRECAUTIONS

General

If irritation or sensitivity develops with the use of clotrimazole, treatment should be discontinued and appropriate therapy instituted.

Information for Patient

This information is intended to aid in the safe and effective use of this medication. It is not a disclosure of all possible adverse or intended effects.

The patient should be advised to:

1. Use the medication for the full treatment time even though the symptoms may have improved. Notify the physician if there is no improvement after 4 weeks of treatment.
2. Inform the physician if the area of application shows signs of increased irritation (redness, itching, burning, blistering, swelling, oozing) indicative of possible sensitization.
3. Avoid sources of infection or reinfection.

Laboratory Tests

If there is lack of response to clotrimazole, appropriate microbiological studies should be repeated to confirm the diagnosis and rule out other pathogens before instituting another course of antimycotic therapy.

Drug Interactions

Synergism or antagonism between clotrimazole and nystatin, or amphotericin B, or flucytosine against strains of C. albicanshas not been reported.

Carcinogenesis, Mutagenesis, and Impairment of Fertility

An 18-month oral dosing study with clotrimazole in rats has not revealed any carcinogenic effect.

In tests for mutagenesis, chromosomes of the spermatophores of Chinese hamsters which had been exposed to clotrimazole were examined for structural changes during the metaphase.

Prior to testing, the hamsters had received five oral clotrimazole doses of 100 mg/kg body weight. The results of this study showed that clotrimazole had no mutagenic effect.

Usage in Pregnancy

The disposition of^14C-clotrimazole has been studied in humans and animals. Clotrimazole is very poorly absorbed following dermal application or intravaginal administration to humans. (See CLINICAL PHARMACOLOGY)

In clinical trials, use of vaginally applied clotrimazole in pregnant women in their second and third trimesters has not been associated with ill effects.

There are, however, no adequate and well-controlled studies in pregnant women during the first trimester of pregnancy.

Studies in pregnant rats with intravaginaldoses up to 100 mg/kg have revealed no evidence of harm to the fetus due to clotrimazole.

High oraldoses of clotrimazole in rats and mice ranging from 50 mg/kg to 120 mg/kg resulted in embryotoxicity (possibly secondary to maternal toxicity), impairment of mating, decreased litter size and number of viable young and decreased pup survival to weaning. However, clotrimazole was notteratogenic in mice, rabbits and rats at oral doses up to 200 mg/kg, 180 mg/kg and 100 mg/kg, respectively. Oral absorption in the rat amounts to approximately 90% of the administered dose.

Because animal reproduction studies are not always predictive of human response, this drug should be used only if clearly indicated during the first trimester of pregnancy.

Nursing Mothers

It is not known whether this drug is excreted in human milk. Because many drugs are excreted in human milk, caution should be exercised when clotrimazole is used by a nursing woman.

Pediatric Use

Safety and effectiveness in pediatric patients have been established for clotrimazole when used as indicated and in the recommended dosage.

ADVERSE REACTIONS

The following adverse reactions have been reported in connection with the use of clotrimazole: erythema, stinging, blistering, peeling, edema, pruritius, urticaria, burning, and general irritation of the skin.

To report SUSPECTED ADVERSE REACTIONS, contact AARNA USA INC. 1-877-225-6999. or FDA at 1-800-FDA-1088 or www.fda.gov/medwatch.

OVERDOSAGE

Acute overdosage with topical application of clotrimazole is unlikely and would not be expected to lead to a life-threatening situation.

DOSAGE AND ADMINISTRATION

Gently spray sufficient Clotrimazole Topical Solution, USP 1% spray into the affected and surrounding skin areas twice a day, in the morning and evening.

Clinical improvement, with relief of pruritus, usually occurs within the first week of treatment with Clotrimazole Topical Solution, USP 1% Spray. If the patient shows no clinical improvement after 4 weeks of treatment with Clotrimazole Topical Solution, USP 1% spray the diagnosis should be reviewed.

HOW SUPPLIED

Clotrimazole Topical Solution, USP 1% Spray is supplied as follows:

NDC 82568-0036-1 in one 10 mL round bottle in a carton
NDC 82568-0036-3 in one 30 mL round bottle in a carton
NDC 82568-0036-6 in two 30 mL round bottles in a carton

STORAGE AND HANDLING

Store at 20° to 25°C (68° to 77°F) [see USP Controlled Room Temperature].

Manufactured for:

AARNA USA INC.

Leland, NC 28451 USA

PRINCIPAL DISPLAY PANEL - 10 mL Round Container label

NDC 82568-0036-1

Clotrimazole
Topical Solution,
USP

1% Spray.

FOR EXTERNAL USE ONLY.
NOT FOR OPHTHALMIC USE.

10 mL Rx Only

Aarna USA Inc

PRINCIPAL DISPLAY PANEL - 30 mL Round Container label

NDC 82568-0036-3

Topical Solution,
USP

1% Spray.

FOR EXTERNAL USE ONLY.
NOT FOR OPTHALMIC USE.

Keep this and all medications out of
reach of children.

30 mL Rx Only

Aarna USA Inc

PRINCIPAL DISPLAY PANEL - 30 mL Carton label

NDC 82568-0036-3

Clotrimazole
Topical Solution, USP

1% Spray

FOR EXTERNAL USE ONLY.
NOT FOR OPHTHALMIC USE.

Keep this and all medications out of
the reach of children.

30 mL Rx Only

Aarna USA Inc.

PRINCIPAL DISPLAY PANEL - 2 x 30 mL Carton label

NDC 82568-0036-6

Clotrimazole
Topical Solution, USP

1% Spray

FOR EXTERNAL USE ONLY.
NOT FOR OPHTHALMIC USE.

Keep this and all medications out of the reach of children.

2 x 30 mL Rx Only

Aarna USA Inc.